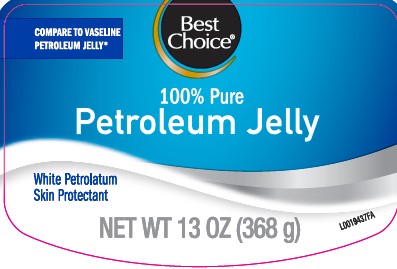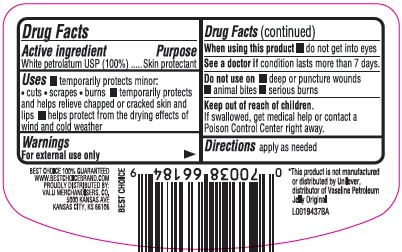 DRUG LABEL: Pure petroleum
NDC: 63941-069 | Form: JELLY
Manufacturer: Valu Merchandisers Company
Category: otc | Type: HUMAN OTC DRUG LABEL
Date: 20260216

ACTIVE INGREDIENTS: PETROLATUM 1 g/1 g

Best Choice 069.001/069AA
Petroleum Jelly

active ingredient

White Petrolatum USP (100%)

Purpose

Skin protectant

Uses

- temporarily protects minor: cuts, scrapes, burns
- temporarily protects and helps relieve chapped or cracked skin and lips
- helps protect from the drying effects of wind and cold weather

Warnings

For external use only

When using this product

- do not get into eyes

See a doctor if

condition lasts more than 7 days

Do not use

- deep or puncture wounds
- animal bites
- serious burns

Keep out of reach of children.

If swallowed, get medical help or contact a Poison Control Center right away.

Directions

apply as needed

Inactive Ingredient

None

Dislcaimer

*This product is not manufactured or distributed by Unliever, distributor of Vaseline Petroleum Jelly Original

Adverse Reactions

BEST CHOICE 100% GUARANTEED

WWW.BESTCHOICEBRAND.COM

PROUDLY DISTRIBUTED BY:

VALU MERCHANDISERS, CO.

5000 KANSAS AVE

KANSAS CITY, KS 66106

BEST CHOICE

principal display panel

Best Choice®

COMPARE TO VASELINE PETROLEUM JELLY*

100% Pure

Petroleum Jelly

White Petrolatum

Skin Protectant

NET WT 13 OZ (368 g)